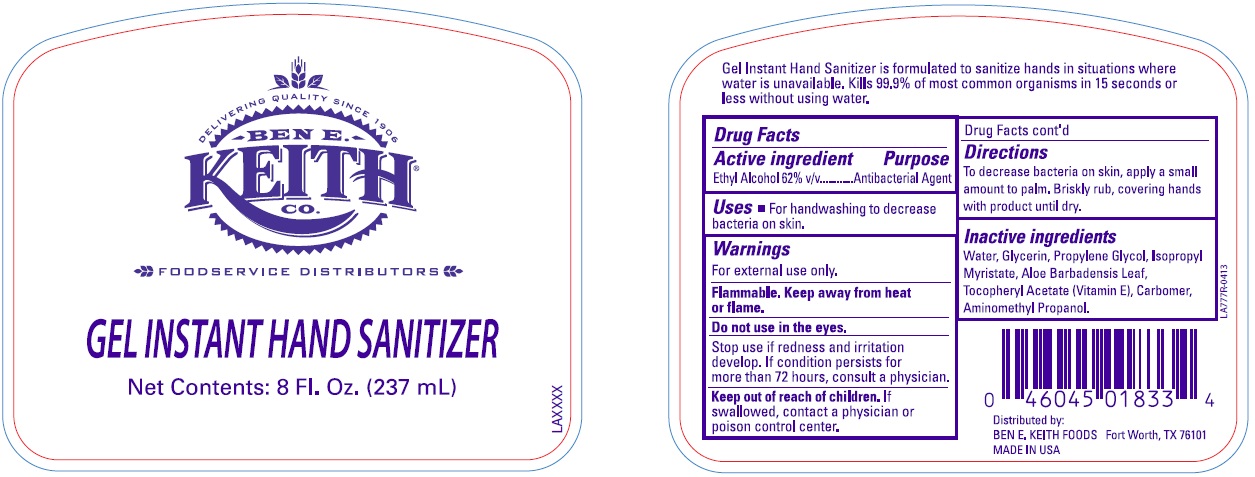 DRUG LABEL: Ben E.Keith
NDC: 50980-056 | Form: GEL
Manufacturer: Ben E. Keith
Category: otc | Type: HUMAN OTC DRUG LABEL
Date: 20250123

ACTIVE INGREDIENTS: ALCOHOL 62 mL/100 mL
INACTIVE INGREDIENTS: WATER; GLYCERIN; PROPYLENE GLYCOL; ISOPROPYL MYRISTATE; ALOE VERA LEAF; .ALPHA.-TOCOPHEROL ACETATE; CARBOMER 1342; AMINOMETHYLPROPANOL

Drug Facts

Active Ingredient

Ethyl Alcohol 62% v/v

Purpose

Antibacterial Agent

Uses

For handwashing to decrease bacteria on skin.

Warnings

For external use only

Flammable Keep away from heat or flame.

Do not use in Eyes

Stop use if redness and irritation develop. If condition persists for more than 72 hours, consult a physician.

Stop use if redness and irritation develop. If condition persists for more than 72 hours, consult a physician.

Keep out of reach of children. If swallowed, contact a physician or poison control center.

Directions

To decrease bacterial on skin, apply a small amount to palm. Briskly rub, covering hands withproduct until dry.

Inactive ingredients

Water, glycerin, propylene glycol, isopropyl myristate, aloe barbadensis leaf, tocopheryl acetate (Vitamin E), Carbomer, Aminomethyl propanol.

Principal Display Panel and representative label

DELIVERING QUALITY SINCE 1906

BEN E.

KEITH

CO.

FOODSERVICE DISTRIBUTORS

GEL INSTANT HAND SANITIZER

Net Contents: 8 Fl. Oz. (237 mL)

Distributed by:

BEN E. KEITH FOODS Fort Worth, TX 76101

MADE IN USA